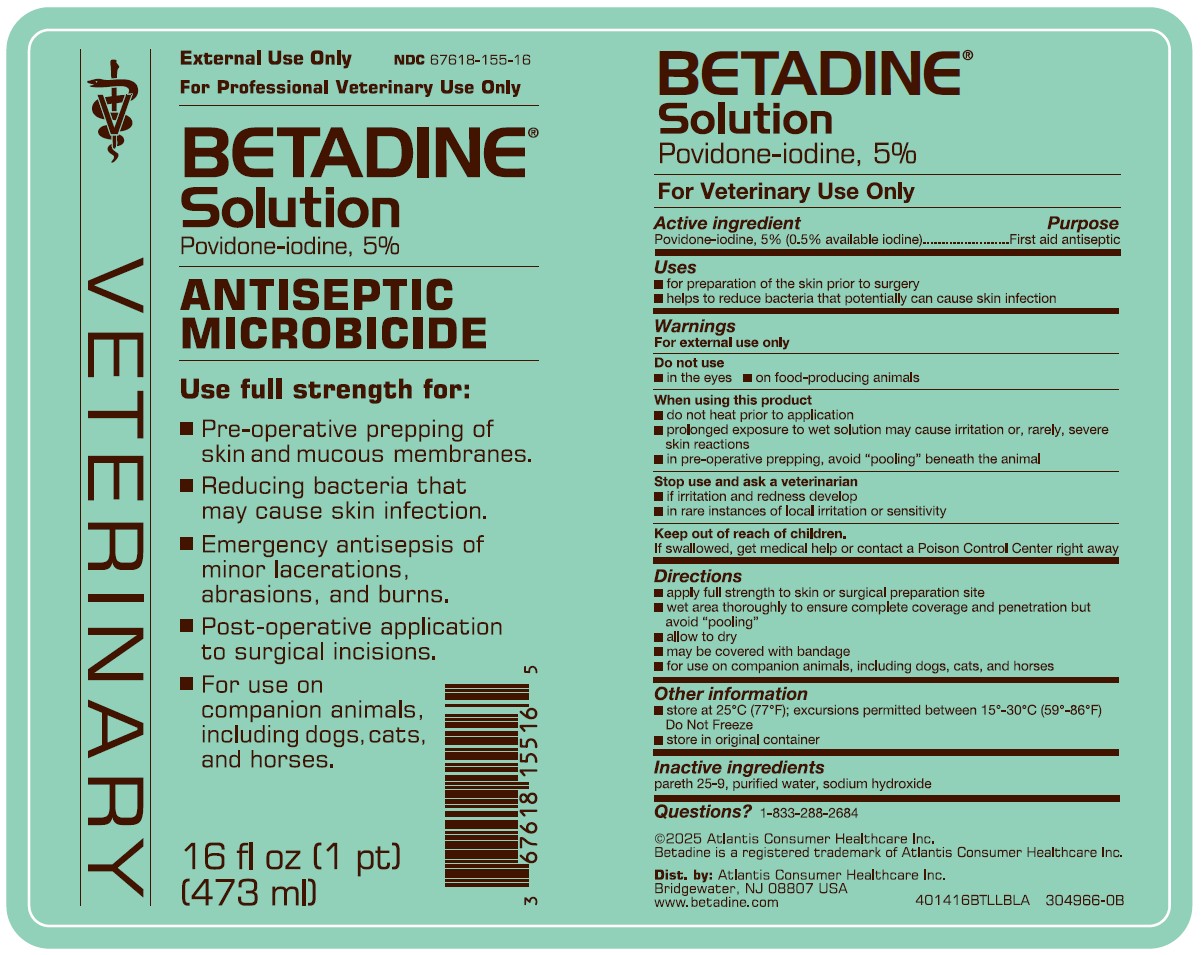 DRUG LABEL: Betadine
NDC: 67618-155 | Form: SOLUTION
Manufacturer: Atlantis Consumer Healthcare Inc
Category: animal | Type: OTC ANIMAL DRUG LABEL
Date: 20251229

ACTIVE INGREDIENTS: Povidone-Iodine 5 mg/1 mL
INACTIVE INGREDIENTS: C12-15 Pareth-9; Water; Sodium Hydroxide

BETADINE® Solution
Povidone-iodine, 5%
For Veterinary Use Only

Active ingredient

Povidone-iodine. 5% (0.5% available iodine)

Purpose

First aid antiseptic

Uses

- for preparation of the skin prior to surgery
- helps to reduce bacteria that potentially can cause skin infection

Warnings

For external use only

Do not use

- in the eyes
- on food-producing animals

When using this product

- do not heat prior to application
- prolonged exposure to wet solution may cause irritation or, rarely, severe skin reactions
- in pre-operative prepping, avoid "pooling" beneath the animal

Stop use and ask a veterinarian

- if irritation and redness develop
- in rare instances of local irritation or sensitivity

Keep out of reach of children.

If swallowed, get medical help or contact a Poison Control Center right away

Directions

- apply full strength to skin or surgical preparation site
- wet area thoroughly to ensure complete coverage and penetration but avoid "pooling"
- allow to dry
- may be covered with bandage
- for use on companion animals, including dogs, cats, and horses

Other Information

- store at 25"C (77°F); excursions permitted between 15"-30"C (59°-86°F) Do Not Freeze
- store in original container

Inactive Ingredients

pareth 25-9, purified water, sodium hydroxide

Questions?

1-833-288-2684
©2025 Atlantis Consumer Healthcare Inc.
Betadine is a registered trademark of Atlantis Consumer Healthcare Inc.
Dist. by: Atlantis Consumer Healthcare Inc.
Bridgewater, NJ 08807 USA
www.betadine.com

Package Label

External Use Only NDC 67618-155-16
For Professional Veterinary Use Only
BETADINE®
Solution
Povidone-iodine, 5%
ANTISEPTIC
MICROBICIDE
Use full strength for:
■ Pre-operative prepping of skin and mucous membranes.
■ Reducing bacteria that may cause skin infection.
■ Emergency antisepsis of minor lacerations, abrasions, and burns.
■ Post-operative application to surgical incisions.
■ For use on companion animals, including dogs, cats, and horses.
16 fl oz (1 pt)
(473 ml)
VETERINARY
401416BTLLBLA 304966-0B